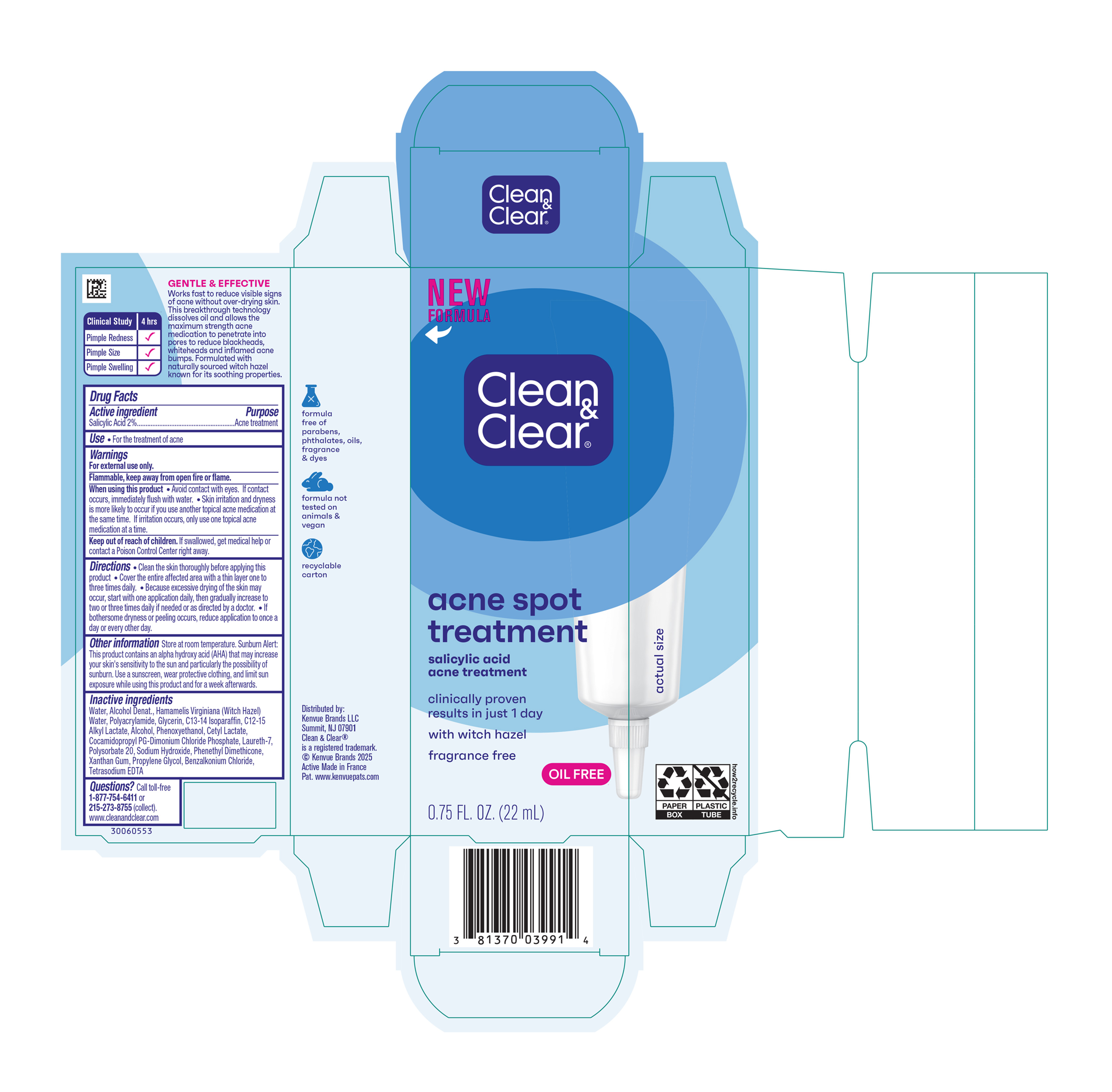 DRUG LABEL: Clean and Clear Acne Spot Treatment
NDC: 69968-0804 | Form: GEL
Manufacturer: Kenvue Brands LLC
Category: otc | Type: HUMAN OTC DRUG LABEL
Date: 20250728

ACTIVE INGREDIENTS: SALICYLIC ACID 20 mg/1 mL
INACTIVE INGREDIENTS: C12-15 ALKYL LACTATE; BENZALKONIUM CHLORIDE; EDETATE SODIUM; WATER; LAURETH-7; CETYL LACTATE; COCAMIDOPROPYL PG-DIMONIUM CHLORIDE PHOSPHATE; POLYSORBATE 20; SODIUM HYDROXIDE; ALCOHOL; HAMAMELIS VIRGINIANA TOP WATER; GLYCERIN; C13-14 ISOPARAFFIN; XANTHAN GUM; PROPYLENE GLYCOL; PHENOXYETHANOL

Clean & Clear® advantage acne spot treatment

Drug Facts

Active Ingredient

Salicylic Acid (2%)

Purpose

Acne treatment

Use

- For the treatment of acne

Warnings

For external use only.

Flammable, keep away from open fire or flame.

When using this product

• Avoid contact with eyes. If contact occurs, immediately flush with water.

• Skin irritation and dryness is more likely to occur if you use another topical acne medication at the same time. If irritation occurs, only use one topical acne medication at a time.

Keep out of reach of children. If swallowed, get medical help or contact a Poison Control Center right away.

Directions

• Clean the skin thoroughly before applying this product

• Cover the entire affected area with a thin layer one to three times daily.

• Because excessive drying of the skin may occur, start with one application daily, then gradually increase to two or three times daily if needed or as directed by a doctor.

• If bothersome dryness or peeling occurs, reduce application to once a day or every other day.

Other Information

Store at room temperature.

Sunburn Alert

This product contains an alpha hydroxy acid (AHA) that may increase your skin’s sensitivity to the sun and particularly the possibility of sunburn. Use a sunscreen, wear protective clothing, and limit sun exposure while using this product and for a week afterwards.

Inactive Ingredients

Water, Alcohol Denat., Hamamelis Virginiana(Witch Hazel) Water, Polyacrylamide, Glycerin, C13-14 Isoparaffin, C12-15 Alkyl Lactate, Alcohol, Phenoxyethanol, Cetyl Lactate, Cocamidopropyl PG-Dimonium Chloride Phosphate, Laureth-7, Polysorbate 20, Sodium Hydroxide, Phenethyl Dimethicone, Xanthan Gum, Propylene Glycol, Benzalkonium Chloride, Tetrasodium EDTA

Questions?

Call toll-free 1-877-754-6411 or 215-273-8755 (collect). www.cleanandclear.com

Distributed by:

Kenvue Brands LLC
Summit, NJ 07901

PRINCIPAL DISPLAY PANEL - 22 mL Tube Carton

NEW

FORMULA

Clean

&

Clear®

acne spot

treatment

salicylic acid

acne treatment

clinically proven

results in just 1 day

with witch hazel

fragrance free

OIL FREE

0.75 FL. OZ. (22 mL)